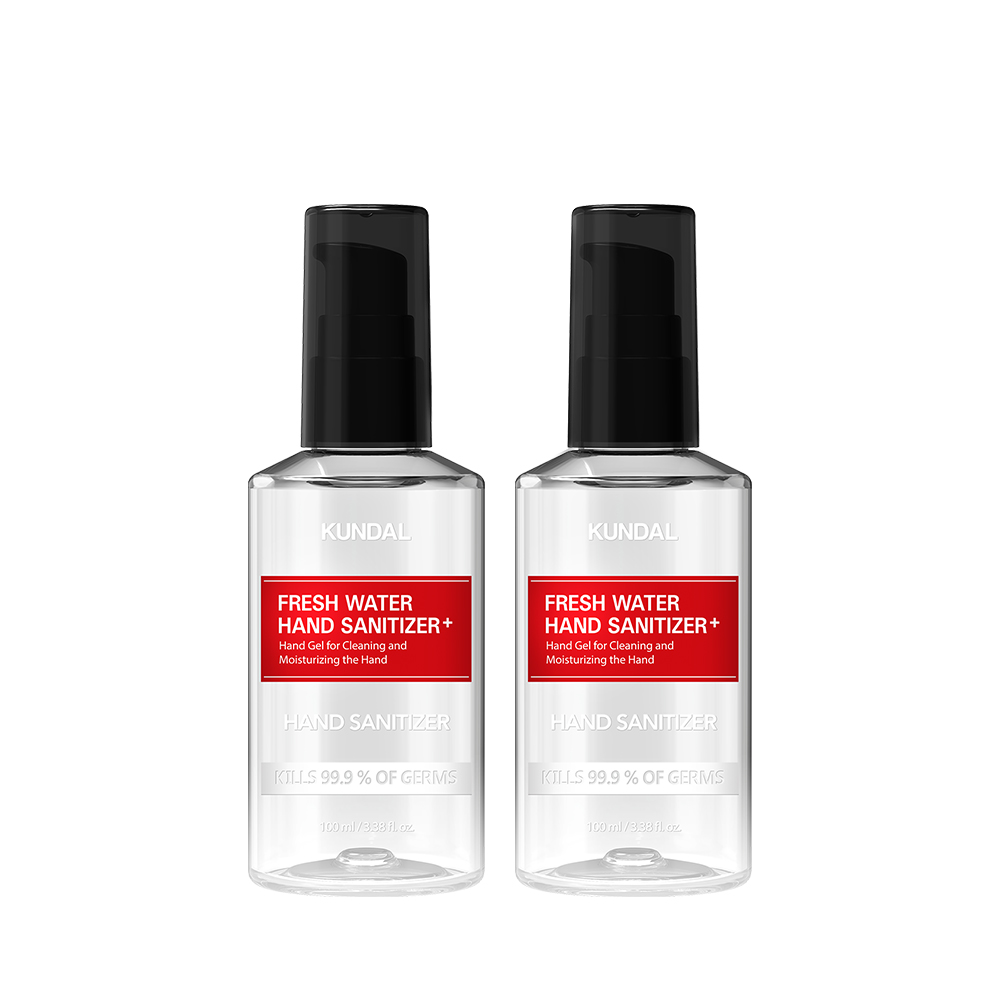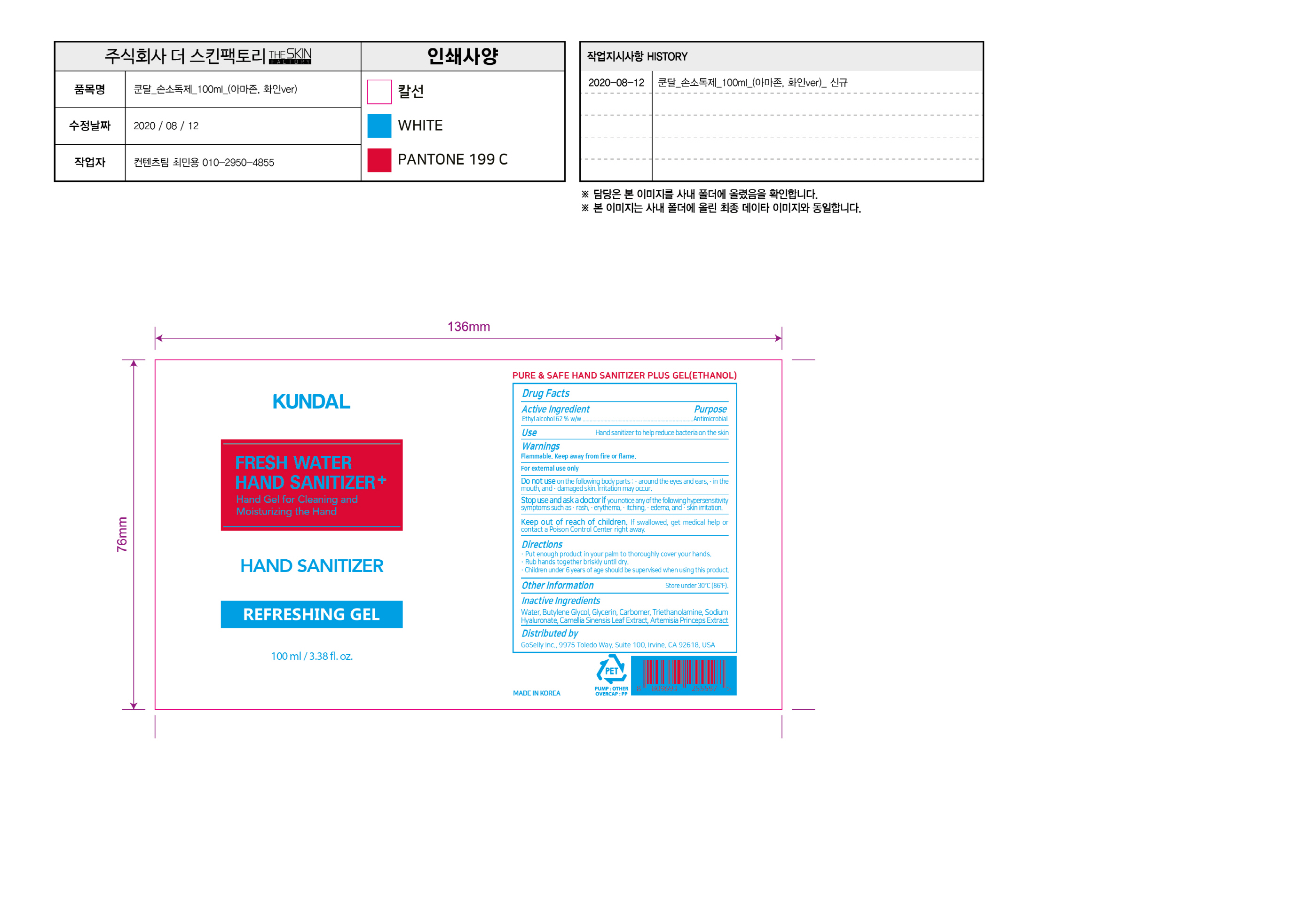 DRUG LABEL: Fresh Water Hand Sanitizer
NDC: 74773-0015 | Form: GEL
Manufacturer: THESKINFACTORY Co., Ltd.
Category: otc | Type: HUMAN OTC DRUG LABEL
Date: 20200818

ACTIVE INGREDIENTS: ALCOHOL 62 g/100 mL
INACTIVE INGREDIENTS: ARTEMISIA PRINCEPS LEAF; BUTYLENE GLYCOL; CARBOMER HOMOPOLYMER, UNSPECIFIED TYPE; GREEN TEA LEAF; TROLAMINE; WATER; GLYCERIN; HYALURONATE SODIUM

Drug Facts

ACTIVE INGREDIENT

Ethyl Alcohol 62% w/w

INACTIVE INGREDIENT

Water, Butylene Glycol, Glycerin, Carbomer, Triethanolamine, Sodium Hyaluronate, Camellia Sinensis Leaf Extract, Artemisia Princeps Extract

PURPOSE

Antiseptic

KEEP OUT OF REACH OF THE CHILDREN

INDICATIONS AND USAGE

Put enough product in your palm to thoroughly cover your hands.

Rub hands together briskly until dry.

Children under 6 years of age should be supervised when using this product.

WARNINGS

For external use only.

Flammable, keep away from fire or flame.

When using this product keep out of eyes. If contact with eyes occurs, rinse promptly and thoroughly with water.

Stop use and ask a doctor if significant irritation or sensitization develops.

Keep out of reach of children. If swallowed, get medical help or contact a Poison Control Center right away.

DOSAGE AND ADMINISTRATION

For external use only